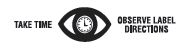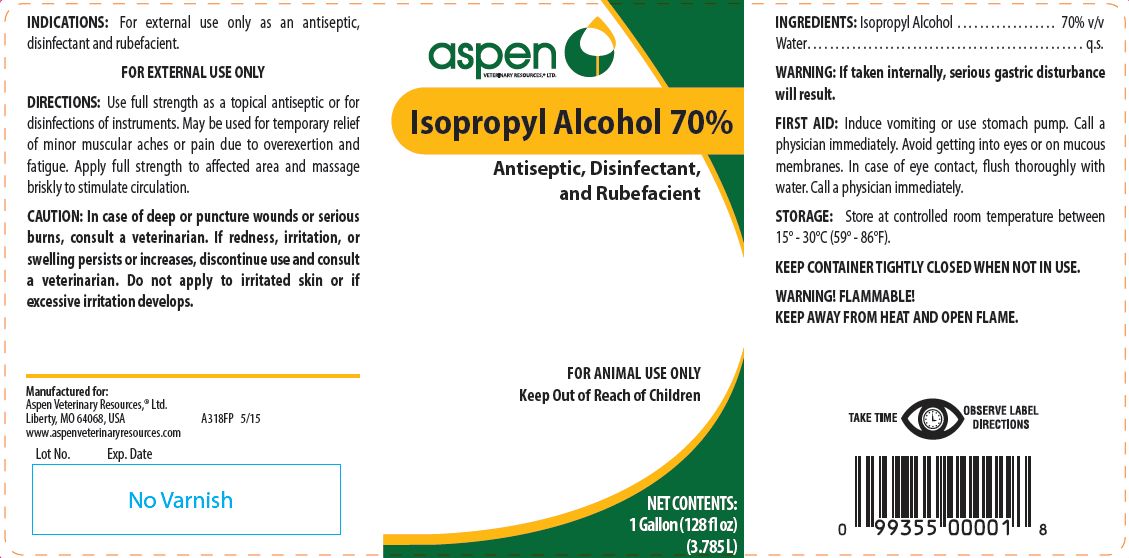 DRUG LABEL: Isopropyl Alcohol
NDC: 46066-231 | Form: SOLUTION
Manufacturer: Aspen Veterinary
Category: animal | Type: OTC ANIMAL DRUG LABEL
Date: 20241029

ACTIVE INGREDIENTS: ISOPROPYL ALCOHOL 557.25 g/1 L

Isopropyl Alcohol 70%

PURPOSE

Antiseptic, Disinfectant, and Rubefacient

KEEP OUT OF REACH OF CHILDREN

FOR ANIMAL USE ONLY
Keep Out of Reach of Children

INDICATIONS:

For external use only as an antiseptic, disinfectant and rubefacient.
FOR EXTERNAL USE ONLY

DIRECTIONS:

Use full strength as a topical antiseptic or for disinfections of instruments. May be used for temporary relief of minor muscular aches or pain due to overexertion and fatigue. Apply full strength to affected area and massage briskly to stimulate circulation.

CAUTION:

In case of deep or puncture wounds or serious burns, consult a veterinarian. If redness, irritation, or swelling persists or increases, discontinue use and consult a veterinarian. Do not apply to irritated skin or if excessive irritation develops.

INGREDIENTS:

Isopropyl Alcohol . . . . . . . . . . . . . . . . . . 70% v/v

INACTIVE INGREDIENT

Water. . . . . . . . . . . . . . . . . . . . . . . . . . . . . . . . . . . . . . . . . . . . . . . . . . q.s.

WARNING:

If taken internally, serious gastric disturbance will result.

FIRST AID:

Induce vomiting or use stomach pump. Call a physician immediately. Avoid getting into eyes or on mucous membranes. In case of eye contact, flush thoroughly with water. Call a physician immediately.

STORAGE:

Store at controlled room temperature between 15° - 30°C (59° - 86°F).
KEEP CONTAINER TIGHTLY CLOSED WHEN NOT IN USE.

WARNINGS

WARNING! FLAMMABLE!
KEEP AWAY FROM HEAT AND OPEN FLAME.

NET CONTENTS:

1 Gallon (128 fl oz) (3.785 L)

INFORMATION FOR OWNERS/CAREGIVERS

Manufactured for:
Aspen Veterinary Resources,® Ltd.
Liberty, MO 64068, USA A318FP 5/15
www.aspenveterinaryresources.com